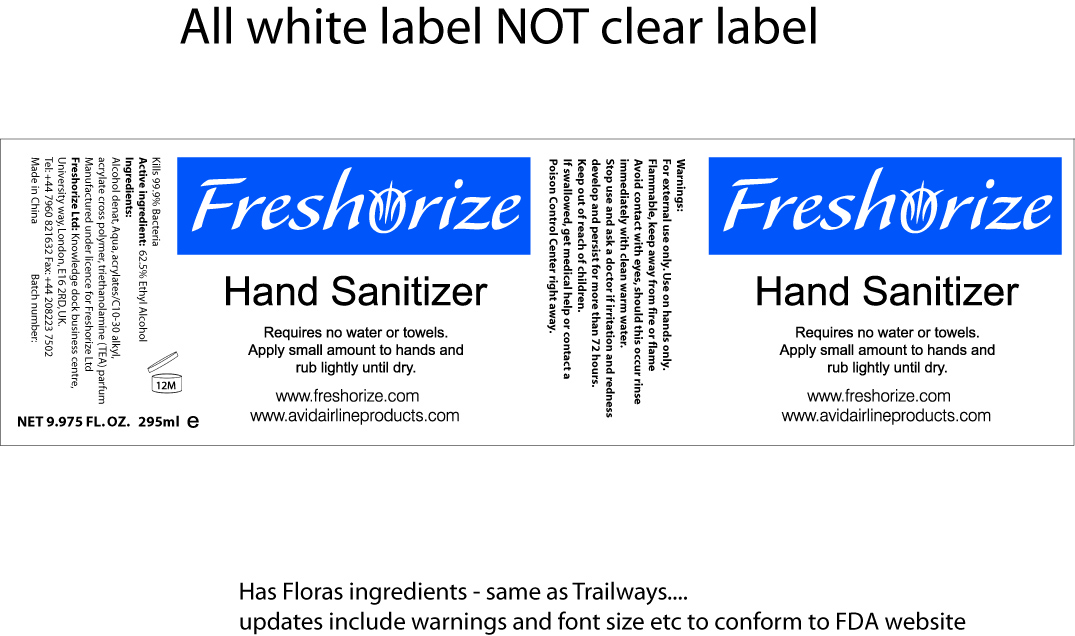 DRUG LABEL: Freshorize
NDC: 52305-200 | Form: LOTION
Manufacturer: Freshorize, Ltd.
Category: otc | Type: HUMAN OTC DRUG LABEL
Date: 20101120

ACTIVE INGREDIENTS: Alcohol 185 mL/295 mL
INACTIVE INGREDIENTS: Water; ETHANOLAMINE

Drug Facts

Active Ingredients

62.5% Ethyl Alcohol.

Use Information

Requires no water or towels. Apply small amount to hands and rub lightly until dry.

WARNINGS

Safety: For External Use Only.Use on Hands only.
Flammable. Keep away from fire or flame.
Avoid contact with Eyes, should this occur rinse immediately with clean warm water.
Stop use and ask a doctor if irritation and redness develop and persist for more than 72 hours.
Keep out of reach of children.
If swallowed, get medical help or contact a Poison Control Center right away.

Display of package label.

Picture of Package Label

Keep out of reach of children

Purpose

Kills 99.9% Bacteria

DOSAGE AND ADMINISTRATION

Requires no water or towels.

Apply small amount to hands and rub lightly until dry.

INACTIVE INGREDIENT

Alcohol denat, Aqua, acrylates/C10-30 alkyl, acrylate cross polymer, triethanolamine (TEA), parfum